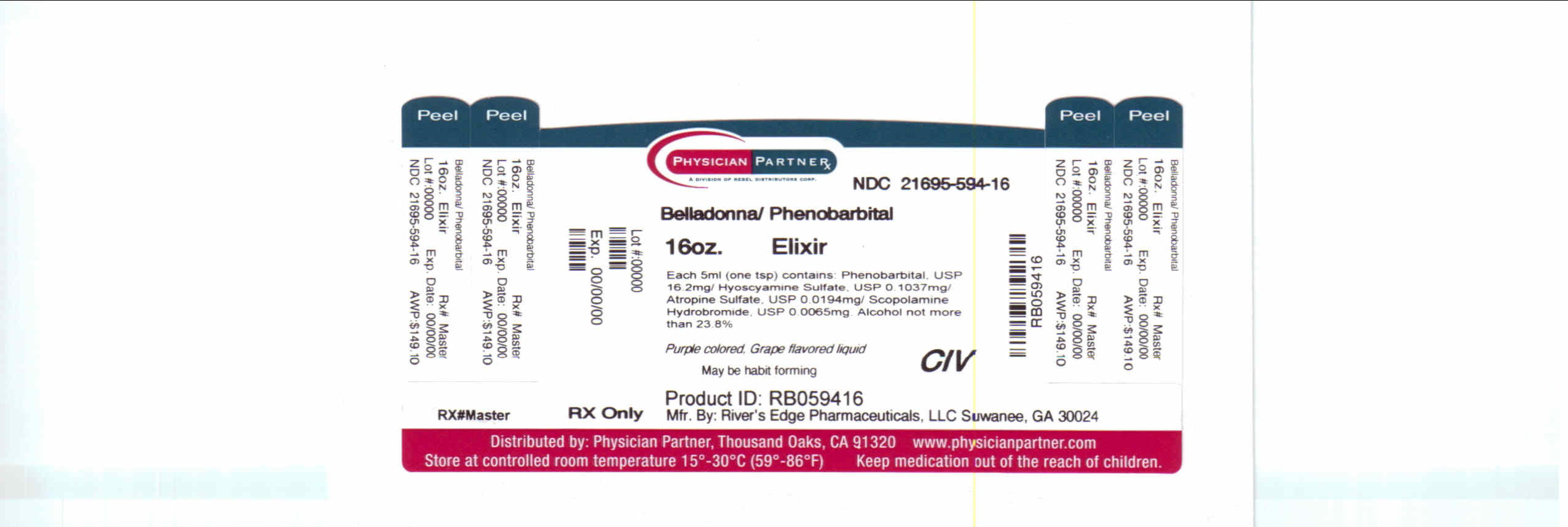 DRUG LABEL: RE-PB HYOS ELIXIR
NDC: 21695-594 | Form: ELIXIR
Manufacturer: Rebel Distributors Corp
Category: prescription | Type: HUMAN PRESCRIPTION DRUG LABEL
Date: 20110126
DEA Schedule: CIV

ACTIVE INGREDIENTS: PHENOBARBITAL 16.2 mg/5 mL; HYOSCYAMINE SULFATE 0.1037 mg/5 mL; ATROPINE SULFATE 0.0194 mg/5 mL; SCOPOLAMINE HYDROBROMIDE 0.0065 mg/5 mL
INACTIVE INGREDIENTS: ALCOHOL; FD&C RED NO. 40; GLYCERIN; WATER; SACCHARIN SODIUM; SORBITOL; SUCROSE

Belladonna/Phenobarbital

DESCRIPTION

Each 5 mL (teaspoonful) of elixir contains:

Phenobarbital, USP ............................................. 16.2 mg
(WARNING: may be habit forming)
Hyoscyamine Sulfate, USP .............................. 0.1037 mg
Atropine Sulfate, USP ..................................... 0.0194 mg
Scopolamine Hydrobromide, USP ................... 0.0065 mg
Alcohol not more than 23.8%

INACTIVE INGREDIENTS:

Artificial Grape Flavor, Ethyl Alcohol, FD and C Blue #1, FD and C Red #40, Glycerin, Purified Water USP, Sodium Saccharin,
Sorbitol Solution 70%, and Sucrose.

CLINICAL PHARMACOLOGY

This drug combination provides peripheral anticholinergic/antispasmodic action and mild sedation.

INDICATION AND USAGE

FDA has classified the following indications as “possibly” effective: For use as adjunctive therapy in the treatment of
irritable bowel syndrome (irritable colon, spastic colon, mucous colitis) and acute enterocolitis. May also be useful as
adjunctive therapy in the treatment of duodenal ulcer.
IT HAS NOT BEEN SHOWN CONCLUSIVELY WHETHER ANTICHOLINERGIC/ ANTISPASMODIC DRUGS AID IN THE
HEALING OF A DUODENAL ULCER, DECREASE THE RATE OF RECURRENCES OR PREVENT COMPLICATIONS.

CONTRAINDICATIONS

RE-PB Hyos Elixir is contraindicated in patients with known hypersensitivity to any of the ingredients. Phenobarbital is
contraindicated in patients with acute intermittent porphyria and in those patients in which phenobarbital produces
restlessness and/or excitement.

It is also contraindicated in patients with glaucoma, obstructive uropathy; paralytic ileus; myasthenia gravis;
intestinal atony; unstable cardiovascular status in acute hemorrhage; hiatal hernia associated with reflux esophagitis;
obstructive disease of the gastrointestinal tract; or severe ulcerative colitis

WARNINGS

Heat prostration can occur with belladonna alkaloids in high temperatures.

Diarrhea may be an early symptom of incomplete intestinal obstruction, especially in patients with ileostomy or colostomy.
In this instance, treatment with this drug could be harmful.

RE-PB Hyos Elixir may produce drowsiness and blurred vision. The patient should be warned about engaging in hazardous work or activities requiring mental alertness, such as operating a motor vehicle or other machinery. Phenobarbital may decrease the effect of anticoagulants, and larger doses of the anticoagulant may be needed for optimal effect. When phenobarbital is discontinued, the dose of the anticoagulant may have to be decreased. Phenobarbital may be habit forming and should not be administered to patients who are susceptible to addiction or to those with a history of physical and/or psychological drug dependence.

Barbiturates should be used with caution in patients with hepatic dysfunction.

PRECAUTIONS

GENERAL:
Use with caution in patients with: autonomic neuropathy, hepatic or renal disease, hyperthyroidism, coronary heart
disease, congestive heart failure, cardiac arrhythmias, tachycardia, and hypertension.

Belladonna alkaloids may produce a delay in gastric emptying (antral stasis) which would complicate the management of
gastric ulcer. Do not rely on the use of the drug in the presence of complication of biliary tract disease. Theoretically,
with overdosage, a curare-like action may occur.

CARCINOGENESIS, MUTAGENESIS, IMPAIRMENT OF FERTILITY:
Long-term studies in animals have not been performed to evaluate carcinogenic potential.

PREGNANCY CATEGORY C:
Animal reproduction studies have not been conducted with RE-PB Hyos Elixir. It is not known whether RE-PB Hyos Elixir
can cause fetal harm when administered to a pregnant woman or can affect reproduction capacity. RE-PB Hyos Elixir
should be given to a pregnant woman only if clearly needed.

NURSING MOTHERS:
It is not known whether this drug is excreted in human milk. Because many drugs are excreted in human milk, caution
should be exercised when RE-PB Hyos Elixir is administered to a nursing woman.

ADVERSE REACTIONS

Adverse reactions associated with anticholinergics and/or anticonvulsants are: dry mouth; tachycardia; urinary
hesitancy and retention; palpitation; blurred vision; prolonged pupil dilation; cycloplegia; increased ocular tension; loss of
taste sense; headache; nervousness; drowsiness; weakness; dizziness; insomnia; nausea; vomiting; severe allergic
reaction or drug idiosyncrasies, including anaphylaxis, hives and/or other dermal manifestations; decreased sweating; impotence; suppression of lactation; constipation; bloated feeling and musculoskeletal pain. Elderly patients may react
with symptoms of excitement, agitation and drowsiness to even small doses of the drug. Phenobarbital may produce
excitement in some patients, rather than a sedative effect. In patients habituated to barbiturates, abrupt withdrawal may
produce delirium or convulsions.

Call your doctor for medical advice about side effects. You may report side effects to the FDA at 1-800-FDA-1088.

OVERDOSAGE

The signs and symptoms of overdose are headache, nausea, vomiting, blurred vision, dilated pupils, hot and

dry skin, dizziness, dryness of the mouth, difficulty in swallowing, and CNS stimulation. Call your doctor or

local Poison Control Center if overdosage is suspected.

DOSAGE AND ADMINISTRATION

The dosage of RE-PB Hyos Elixir should be adjusted to the needs of the individual patient to assure
symptomatic control with a minimum of adverse effects.

Adults: One or two teaspoonfuls of elixir three or four times a day according to conditions and severity of symptoms.

Pediatric patients: may be dosed every 4 to 6 hours.

Starting Dosage
Body Weight | q4h | q6h
10 lb. (4.5 kg) | 0.5 mL | 0.75 mL
20 lb. (9.1 kg) | 1.0 mL | 1.5 mL
30 lb. (13.6 kg) | 1.5 mL | 2.0 mL
50 lb. (22.7 kg) | 1/2 tsp | 3/4 tsp
75 lb. (34 kg) | 3/4 tsp | 1 tsp
100 lb. (45.4kg) | 1 tsp | 1 1/2 tsp

HOW SUPPLIED

RE-PB Hyos Elixir is a purple colored, grape flavored liquid.

NDC 21695-594-16 in bottles of 16 oz.

WARNINGS: KEEP THIS AND ALL DRUGS OUT OF THE REACH OF CHILDREN. IN CASE OF ACCIDENTAL
OVERDOSE, SEEK PROFESSIONAL ASSISTANCE OR CONTACT A POISON CONTROL CENTER IMMEDIATELY.

Manufactured by:
Great Southern Laboratories
Houston, TX 77099-3405

Manufactured for:
River’s Edge Pharmaceuticals, LLC
Suwanee, GA 30024

Repackaged by:
Rebel Distributors Corp

Thousand Oaks, CA 91320